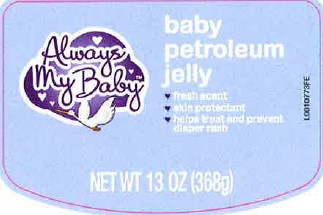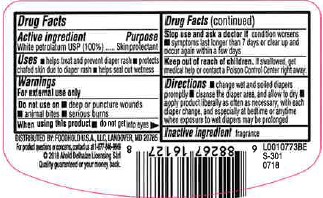 DRUG LABEL: Petrolatum
NDC: 72476-519 | Form: JELLY
Manufacturer: Retail Business Services, LLC
Category: otc | Type: HUMAN OTC DRUG LABEL
Date: 20260206

ACTIVE INGREDIENTS: PETROLATUM 1 g/1 g

Always My Baby 519.001/519AC-AD
Baby Petroleum Jelly

Active ingredient

White petrolatum USP (100%)

Purpose

Skin protectant

Uses

- helps treat and prevent diaper rash
- protects chafed skin due to diaper rash
- helps seal out wetness

Warnings

For external use only

Do not use on

- deep or puncture wounds
- animal bites
- serious burns

When using this product

- do not get into eyes

Stop use and ask a doctor if

condition worsens

- symptoms last longer than 7 days or clear up and occur again within a few days

Keep out of reach of children.

If swallowed, get medical help or contact a Poison Control Center right away.

Directions

- change wet and soiled diapers promptly
- cleanse the diaper area, and allow to dry
- apply product liberally as often as necessary, with each diaper change, and especially at bedtime or anytime when exposure to wet diapers may be prolonged

Inactive ingredient

fragrance

Adverse reactions

DISTRIBUTED BY FOODHOLD U.S.A, LLC, LANDOVER, MD 20785

For product questions or concerns, contact us at 1-877-846-9949

©2018 Ahold Delhaize Licensing Sàrl

Quality guaranteed or your money back.

Principal display panel

Always My Baby™

baby petroleum jelly

- fresh scent
- skin protectant
- helps treat and prevent diaper rash

NET WT 13 oz (368 g)